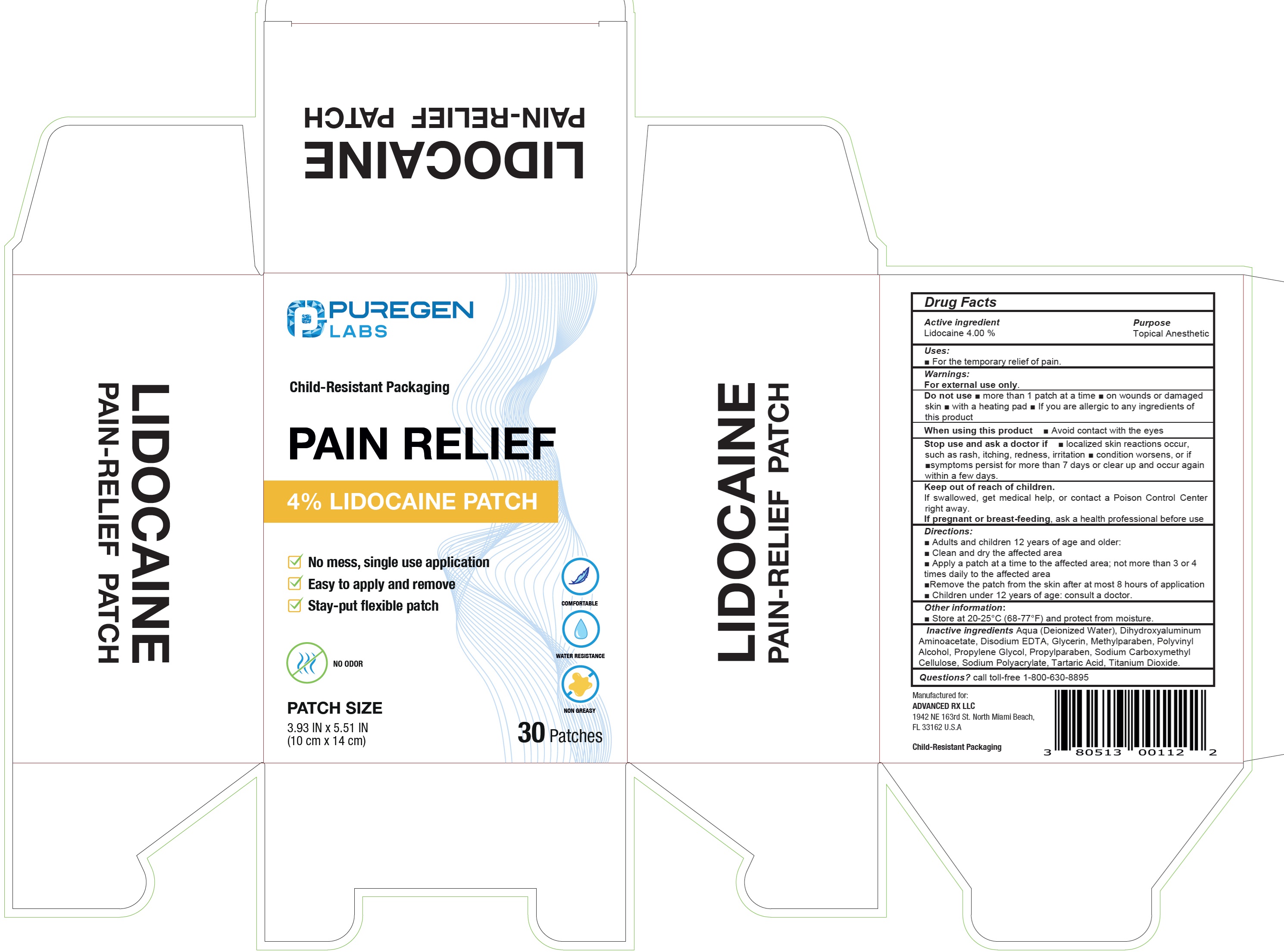 DRUG LABEL: PUREGEN LABS Pain Relief 4 Lidocaine
NDC: 80513-814 | Form: PATCH
Manufacturer: Advanced Rx LLC
Category: otc | Type: HUMAN OTC DRUG LABEL
Date: 20240611

ACTIVE INGREDIENTS: LIDOCAINE 40 mg/1 g
INACTIVE INGREDIENTS: WATER; DIHYDROXYALUMINUM AMINOACETATE; EDETATE DISODIUM; GLYCERIN; METHYLPARABEN; POLYVINYL ALCOHOL, UNSPECIFIED; PROPYLENE GLYCOL; PROPYLPARABEN; CARBOXYMETHYLCELLULOSE SODIUM, UNSPECIFIED; TARTARIC ACID; TITANIUM DIOXIDE

PUREGEN LABS Pain Relief 4% Lidocaine Patch

Active ingredient

Lidocaine 4.00 %

Purpose

Topical Anesthetic

Uses:

- For the temporary relief of pain.

Warnings:

For external use only.

Do not use

- more than 1 patch at a time
- on wounds or damaged skin
- with a heating pad
- If you are allergic to any ingredients of this product

When using this product

- Avoid contact with the eyes

Stop use and ask a doctor if

- localized skin reactions occur, such as rash, itching, redness, irritation
- condition worsens, or if
- symptoms persist for more than 7 days or clear up and occur again within a few days.

Keep out of reach of children.

If swallowed, get medical help, or contact a Poison Control Center right away.

If pregnant or breast-feeding,

ask a health professional before use

Directions:

- Adults andchildren 12 years of age and older:
- Clean and dry the affected area
- Apply a patch at a time to the affected area; not more than 3 or 4 times daily to the affected area
- Remove the patch from the skin after at most 8 hours of application
- Children under 12 years of age: consult a doctor.

Other information:

- Store at 20-25°C (68-77°F) and protect from moisture.

Inactive ingredients

Aqua (Deionized Water), Dihydroxyaluminum Aminoacetate, Disodium EDTA, Glycerin, Methylparaben, Polyvinyl Alcohol, Propylene Glycol, Propylparaben, Sodium Carboxymethyl Cellulose, Sodium Polyacrylate, Tartaric Acid, Titanium Dioxide

Questions?

call toll-free 1-800-630-8895